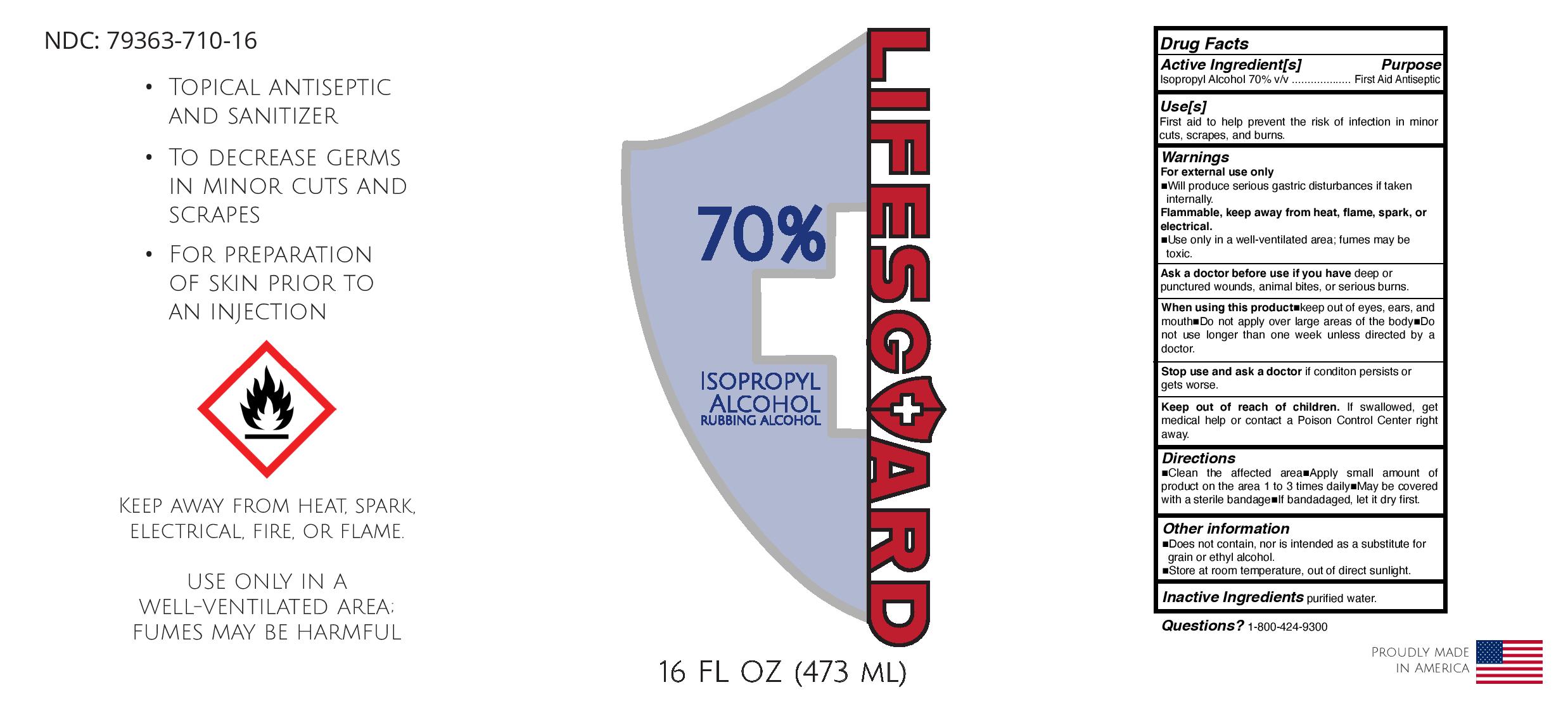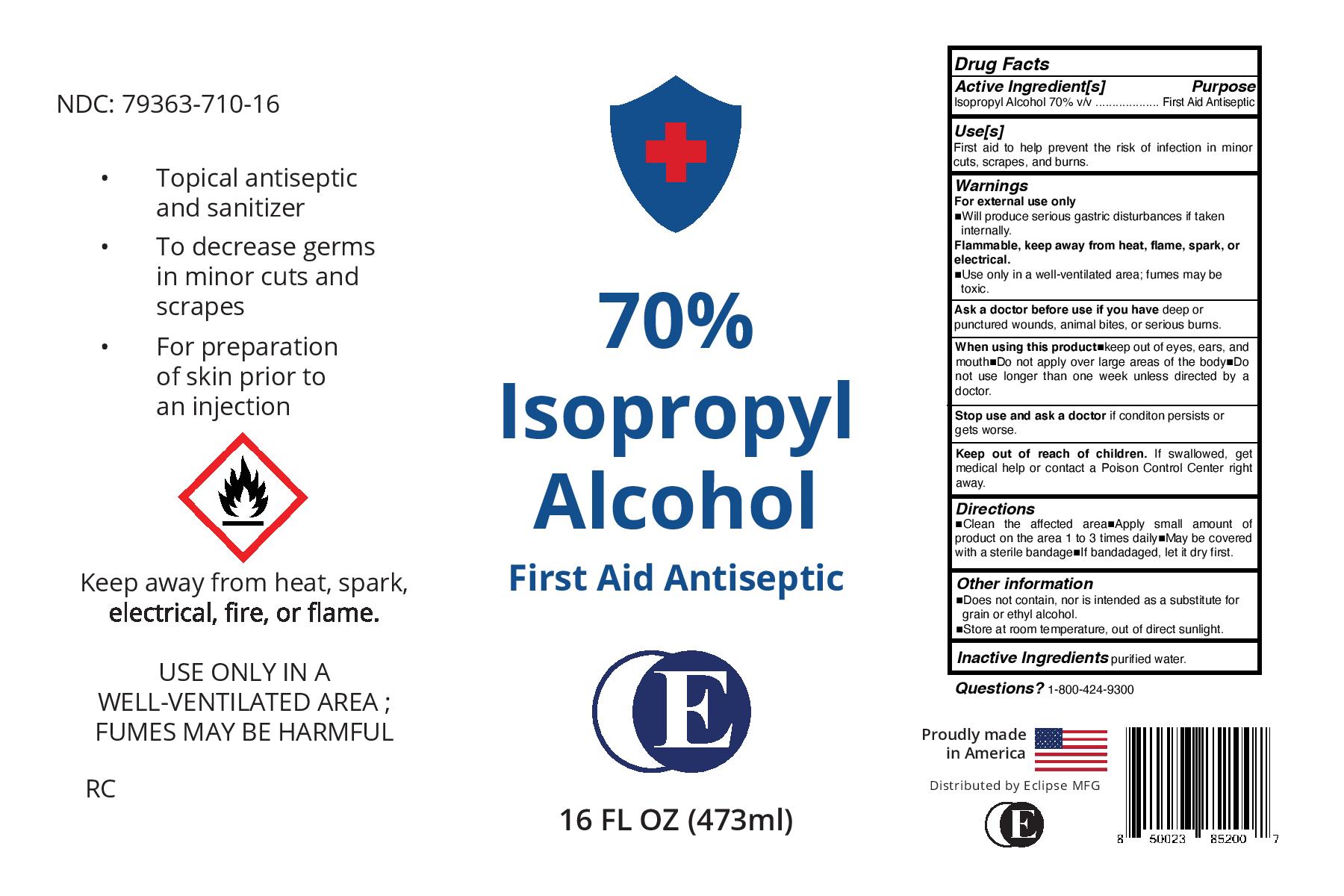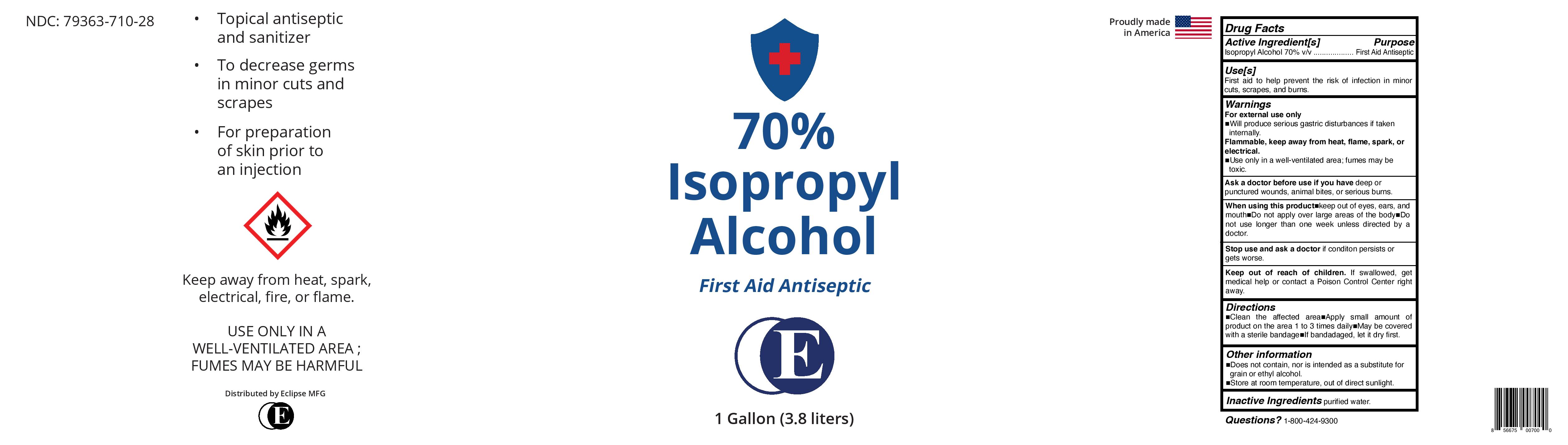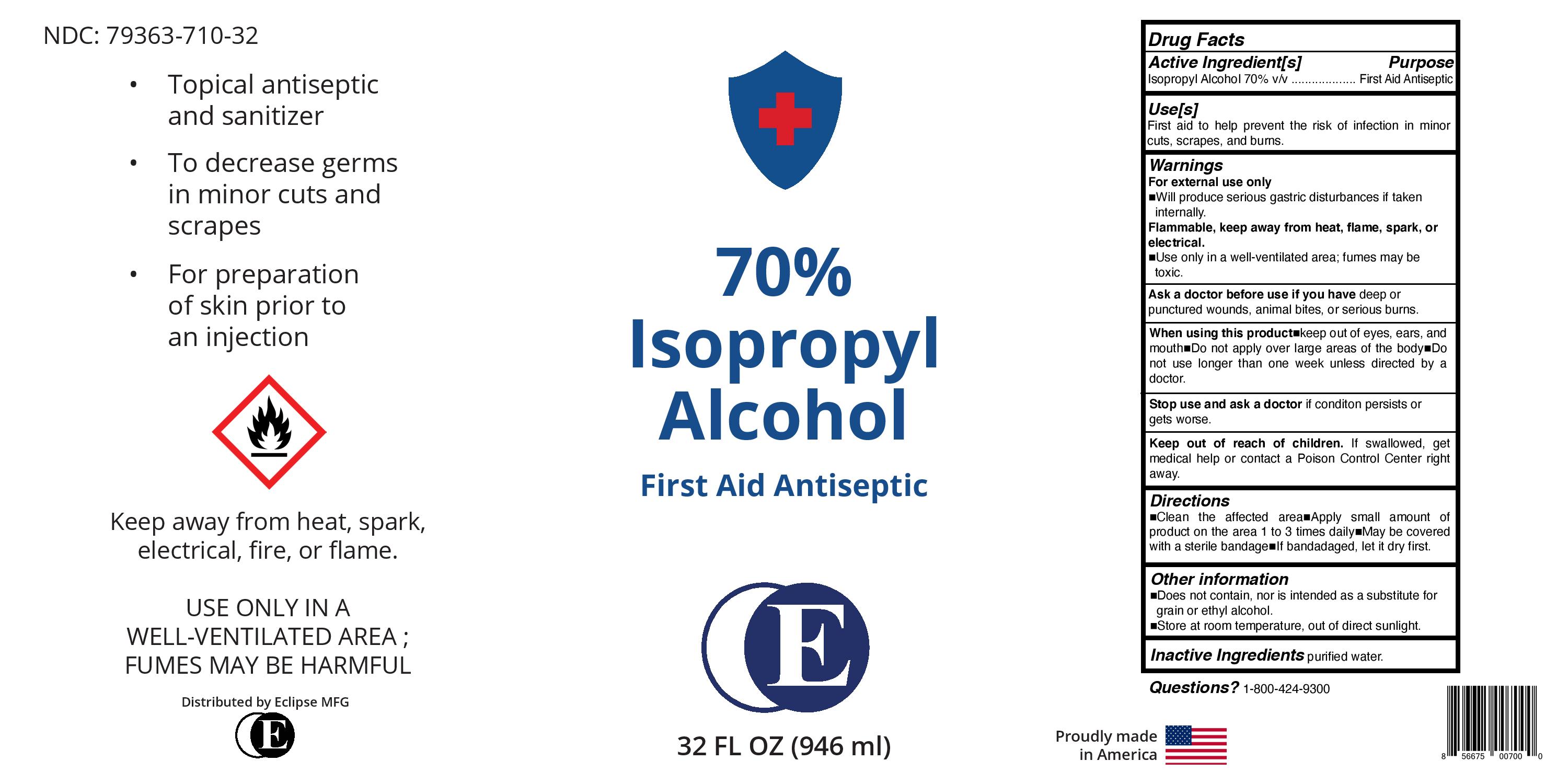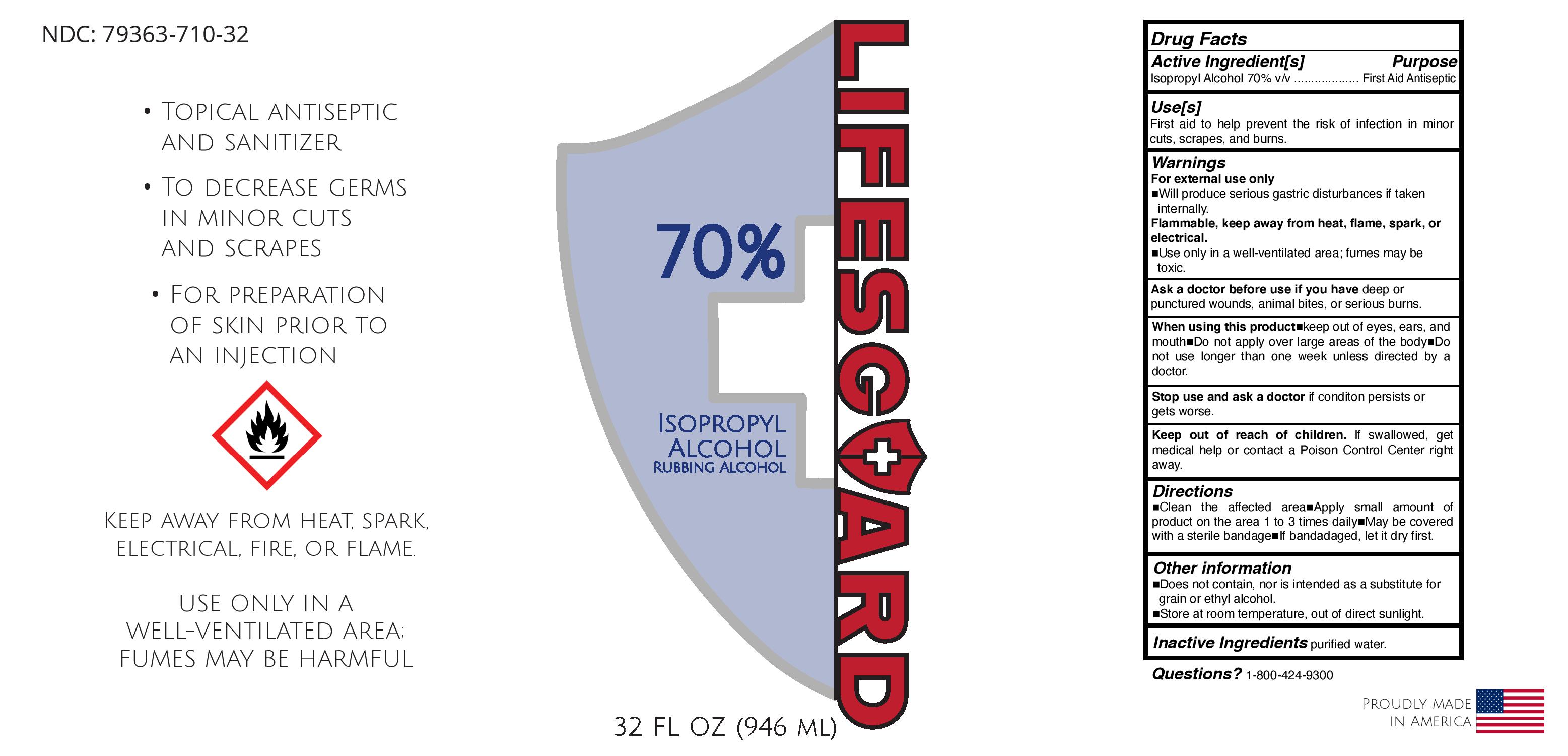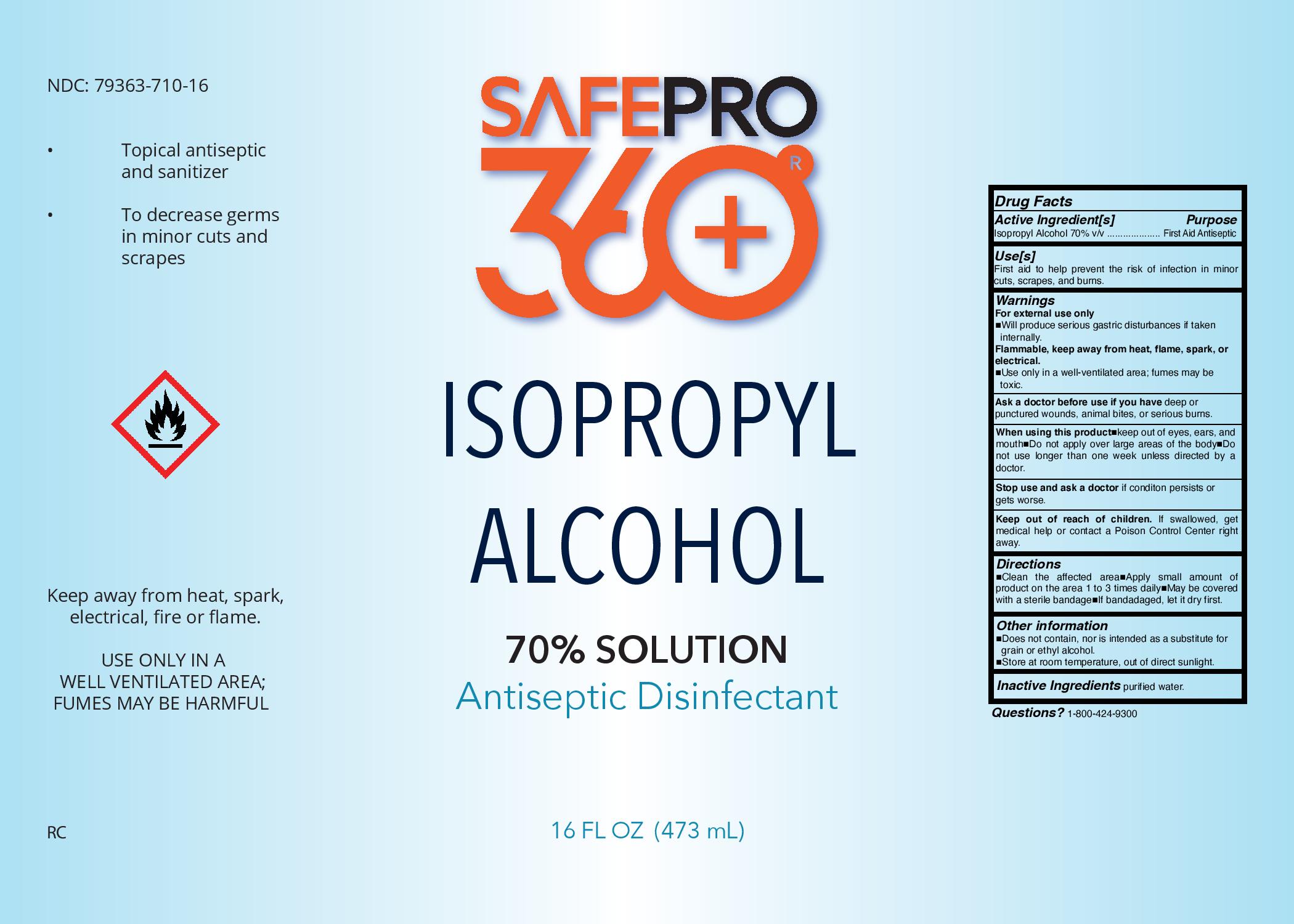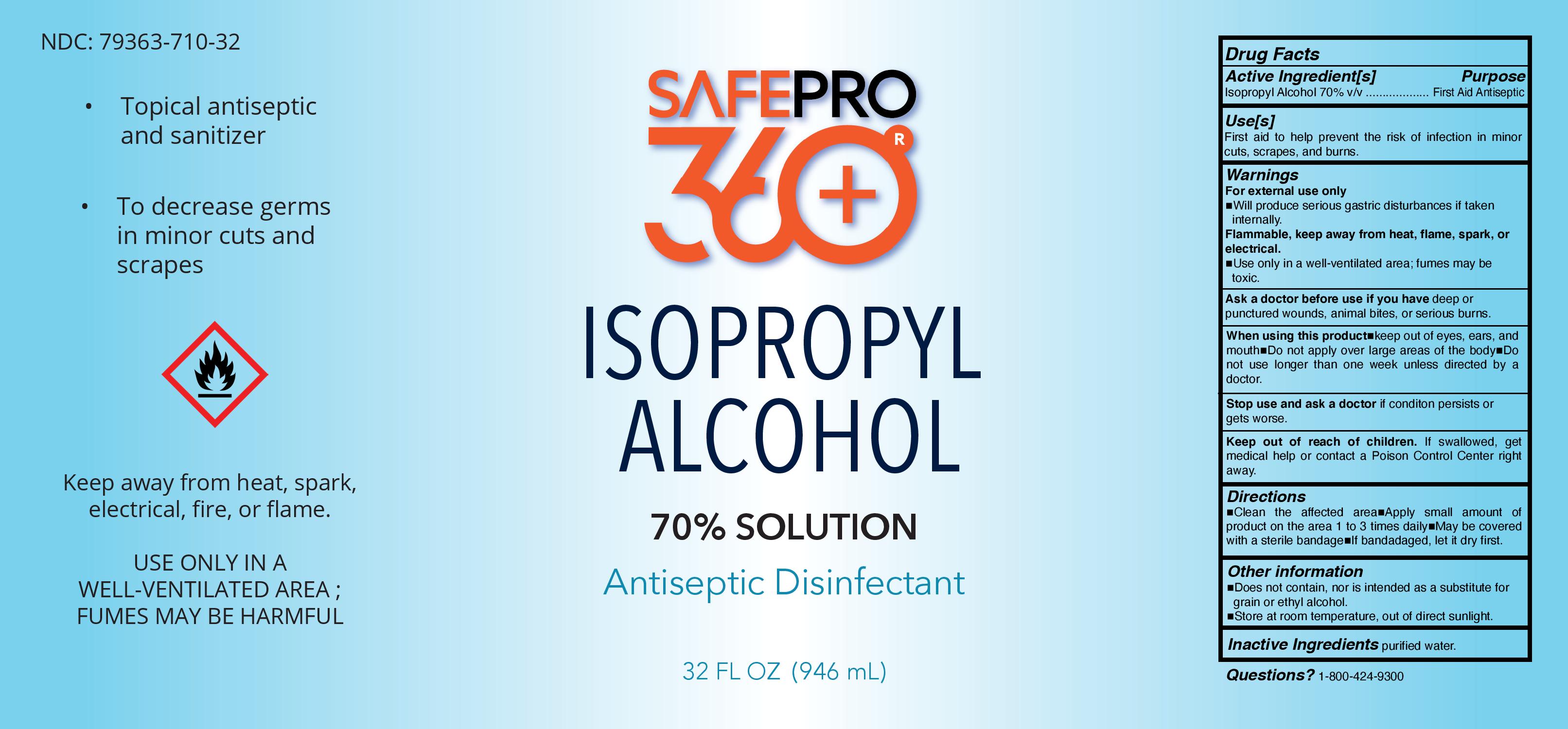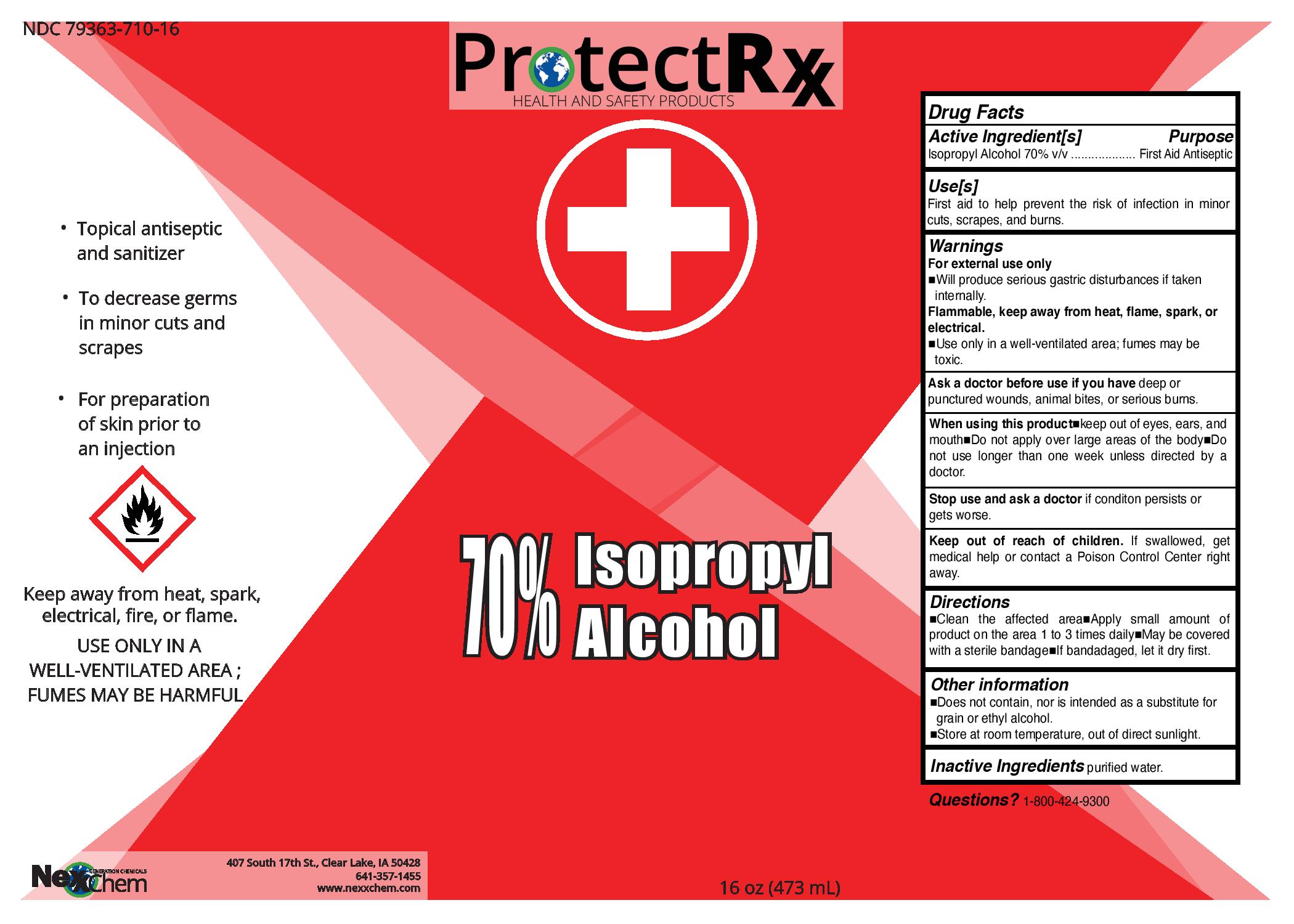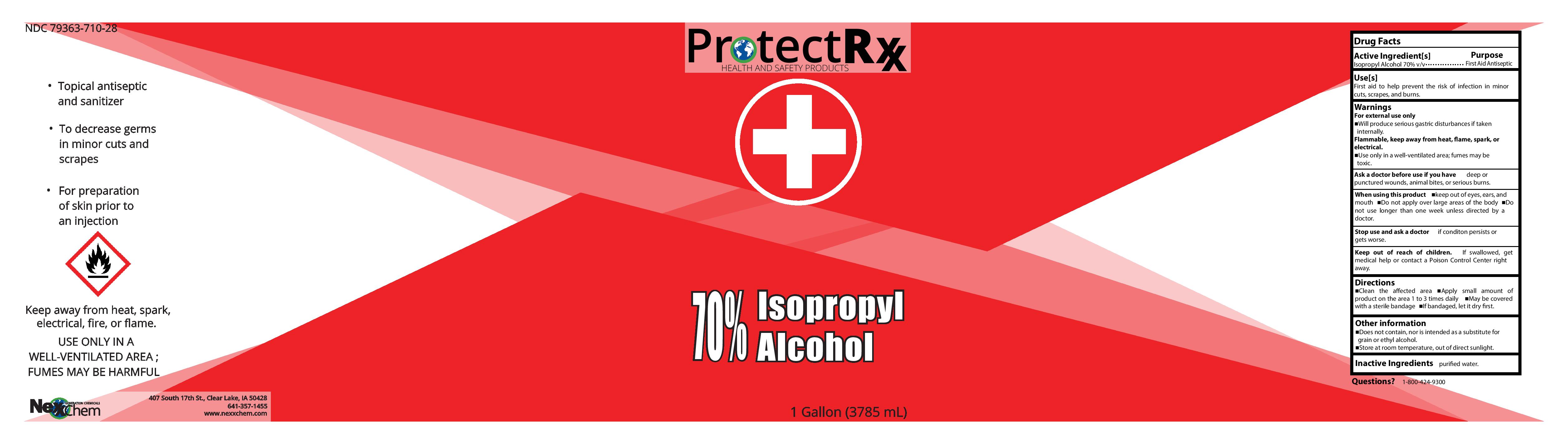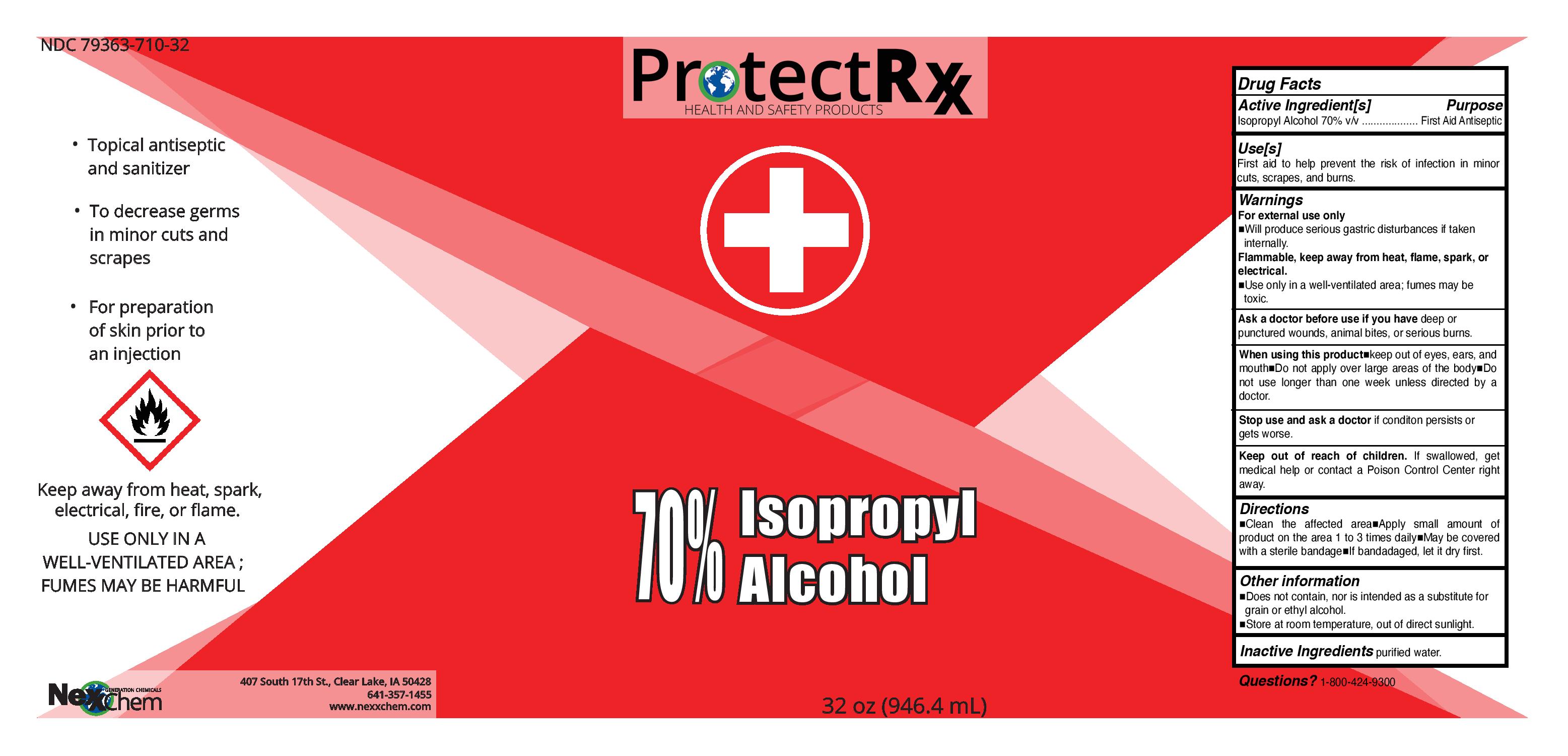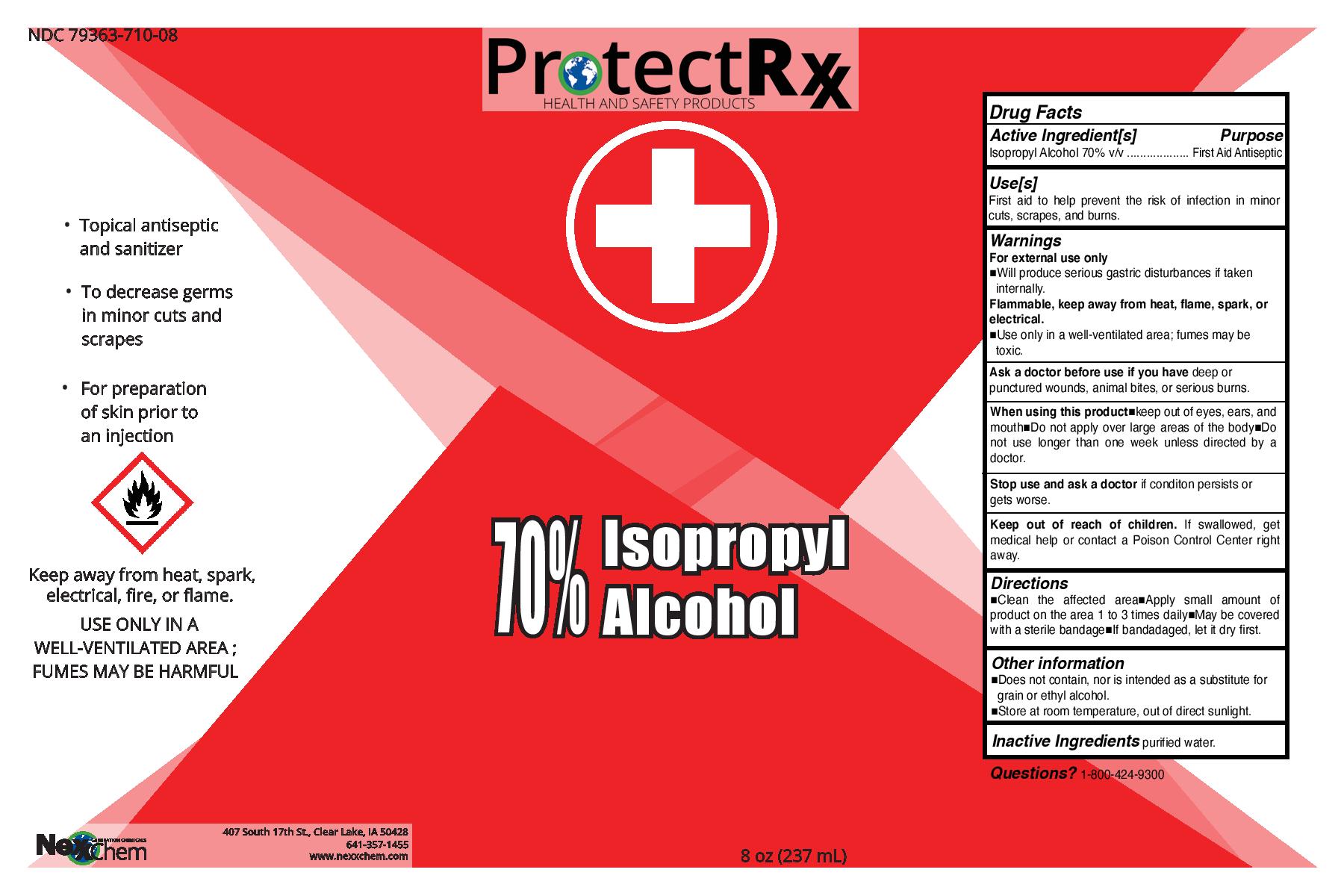 DRUG LABEL: First Aid Antiseptic
NDC: 79363-710 | Form: LIQUID
Manufacturer: REALCHEM MANUFACTURING
Category: otc | Type: HUMAN OTC DRUG LABEL
Date: 20210204

ACTIVE INGREDIENTS: ISOPROPYL ALCOHOL 70 mL/100 mL
INACTIVE INGREDIENTS: WATER

70% IPA Antiseptic

This is a first aid antiseptic manufactured according to FDA Guidance.

Active Ingredient(s)

Isopropyl Alcohol 70% v/v. Purpose: Antiseptic

Purpose

Antiseptic, Hand Sanitizer

Use

Antiseptic to decrease germs in minor cuts and scrapes and for preparation of skin prior to an injection; Hand Sanitizer to help reduce bacteria that potentially can cause disease. For use when soap and water are not available.

Warnings

For external use only. Flammable. Keep away from heat or flame

Do not use

- in children less than 2 months of age
- on open skin wounds

When using this product keep out of eyes, ears, and mouth. In case of contact with eyes, rinse eyes thoroughly with water.
Stop use and ask a doctor if irritation or rash occurs. These may be signs of a serious condition.
Keep out of reach of children. If swallowed, get medical help or contact a Poison Control Center right away.

Stop use and ask a doctor if irritation or rash occurs. These may be signs of a serious condition.

Keep out of reach of children. If swallowed, get medical help or contact a Poison Control Center right away.

Directions

- Clean the affected area; apply small amount of product on the area 1 to 3 times daily.
- Supervise children under 6 years of age when using this product to avoid swallowing.

Other information

- Store between 15-30C (59-86F)
- Avoid freezing and excessive heat above 40C (104F)

Inactive ingredients

purified water USP

Package Label - Principal Display Panel

473 ml NDC: 79363-710-16

946 ml NDC: 79363-710-32

237ml NDC: 79363-710-08

3785ml NDC: 79363-710-28